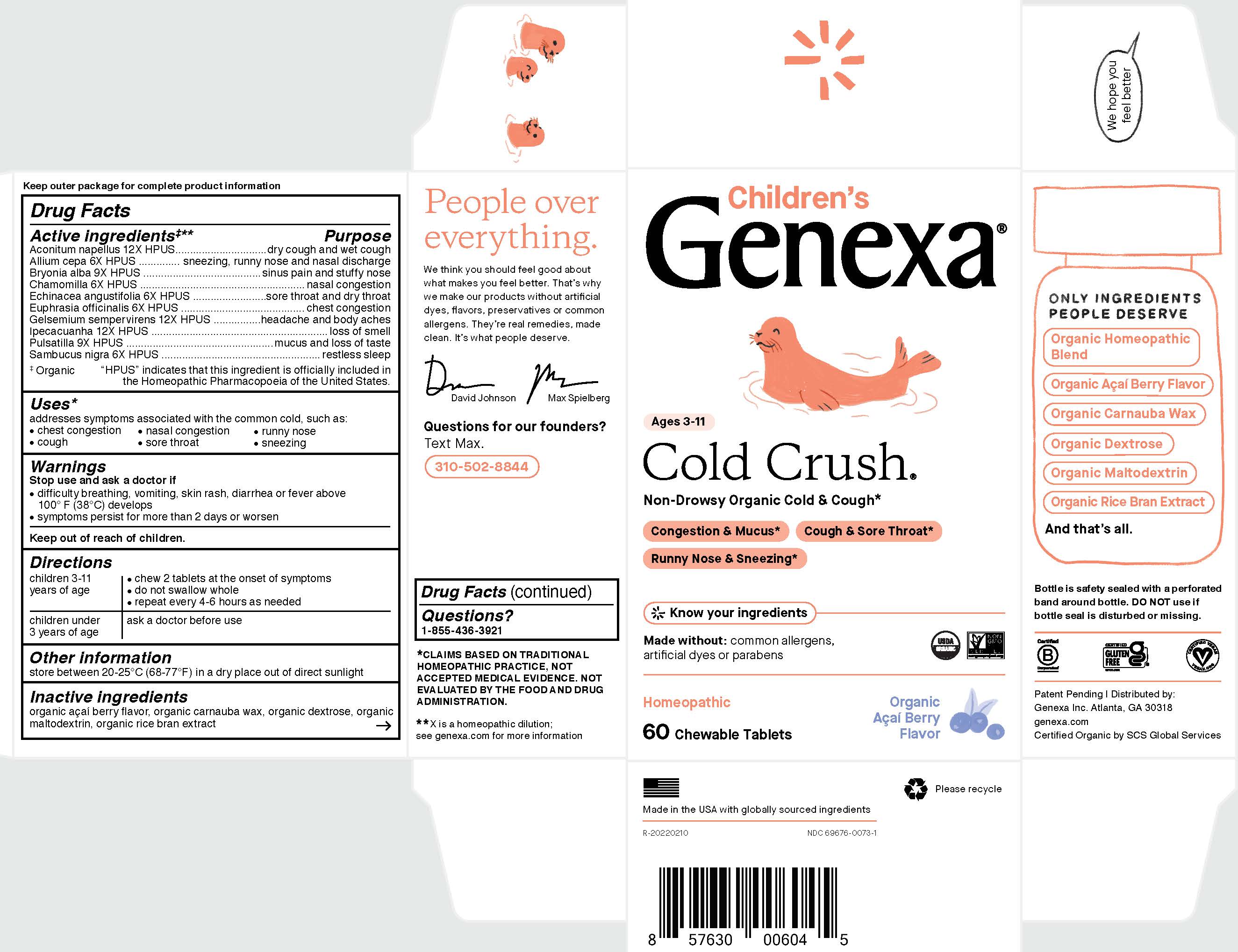 DRUG LABEL: Childrens Cold Crush
NDC: 69676-0073 | Form: TABLET, CHEWABLE
Manufacturer: Genexa Inc.
Category: homeopathic | Type: HUMAN OTC DRUG LABEL
Date: 20250416

ACTIVE INGREDIENTS: BRYONIA ALBA ROOT 9 [hp_X]/1 1; GELSEMIUM SEMPERVIRENS ROOT 12 [hp_X]/1 1; ONION 6 [hp_X]/1 1; MATRICARIA CHAMOMILLA WHOLE 6 [hp_X]/1 1; ECHINACEA ANGUSTIFOLIA 6 [hp_X]/1 1; EUPHRASIA STRICTA 6 [hp_X]/1 1; SAMBUCUS NIGRA FLOWER 6 [hp_X]/1 1; IPECAC 12 [hp_X]/1 1; ACONITUM NAPELLUS 12 [hp_X]/1 1; PULSATILLA PRATENSIS 9 [hp_X]/1 1
INACTIVE INGREDIENTS: CARNAUBA WAX; RICE BRAN; DEXTROSE; MALTODEXTRIN; ACAI

Children's Cold Crush

Drug Facts

Active Ingredients‡**

Aconitum napellus 12X HPUS

Allium cepa 6X HPUS

Bryonia alba 9X HPUS

Chamomilla 6X HPUS

Echinacea angustifolia 6X HPUS

Euphrasia officinalis 6X HPUS

Gelsemium sempervirens 12X HPUS

Ipecacuanha 12X HPUS

Pulsatilla 9X HPUS

Sambucus nigra 6X HPUS

Purpose

dry cough and wet cough

sneezing, runny nose and nasal discharge

sinus pain and stuffy nose

nasal congestion

sore throat and dry throat

chest congestion

headache and body aches

loss of smell

mucus and loss of taste

restless sleep

‡ Organic

"HPUS" indicates that this ingredient is officially included in the Homeopathic Pharmacopoeia of the United States.

Uses*

addresses symptoms associated with the common cold, such as:

- chest congestion
- cough
- nasal congestion
- sore throat
- runny nose
- sneezing

Warnings

Stop use and ask a doctor if

- difficulty breathing, vomiting, skin rash, diarrhea or fever above 100º F (38ºC) develops
- symptoms persist for more than 2 days or worsen

Keep out of reach of children.

Directions

children 3-11 years of age | - chew 2 tablets at the onset of symptoms - do not swallow whole - repeat every 4-6 hours as needed
children under 3 years of age | ask a doctor before use

Other information

store between 20-25ºC (68-77ºF) in a dry place out of direct sunlight

Inactive ingredients

organic açaí berry flavor, organic carnauba wax, organic dextrose, organic maltodextrin, organic rice bran extract

Questions?

1-855-436-3921

*CLAIMS BASED ON TRADITIONAL HOMEOPATHIC PRACTICE, NOT ACCEPTED MEDICAL EVIDENCE. NOT EVALUATED BY THE FOOD AND DRUG ADMINISTRATION.

**X is a homeopathic dilution; see genexa.com for more information

Bottle is safety sealed with a perforated band around bottle. DO NOT use if bottle seal is disturbed or missing.

Patent Pending | Distributed by:

Genexa Inc. Atlanta, GA 30318

genexa.com

Certified Organic by SCS Global Services

Made in the USA with globally sourced ingredients

NDC 69676-0073-1

PACKAGE LABEL

Children's

Genexa®

Ages 3-11

Cold Crush®

Non-Drowsy Organic Cold & Cough*

Congestion & Mucus*

Cough & Sore Throat*

Runny Nose & Sneezing*

Know your ingredients

Made without: common allergens, artificial dyes or parabens

Homeopathic

60 Chewable Tablets

Organic Açaí Berry Flavor